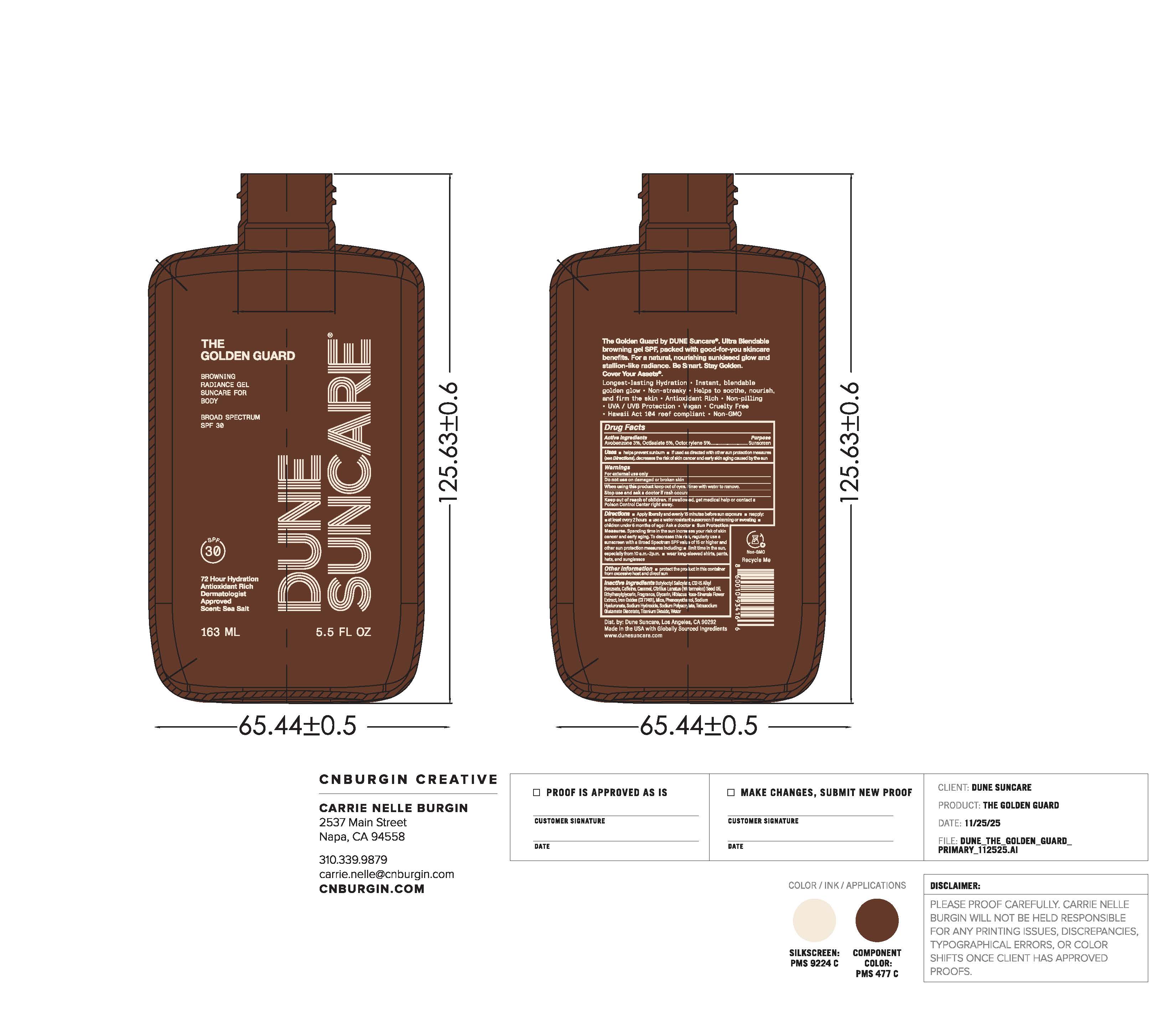 DRUG LABEL: THE GOLDEN GUARD
NDC: 82757-202 | Form: GEL
Manufacturer: Dune Suncare, Inc.
Category: otc | Type: HUMAN OTC DRUG LABEL
Date: 20251219

ACTIVE INGREDIENTS: AVOBENZONE 30 mg/1 mL; OCTISALATE 50 mg/1 mL; OCTOCRYLENE 50 mg/1 mL
INACTIVE INGREDIENTS: HIBISCUS ROSA-SINENSIS FLOWER; MICA; CARAMEL; SODIUM POLYACRYLATE (8000 MW); CAFFEINE; TITANIUM DIOXIDE; BUTYLOCTYL SALICYLATE; C12-15 ALKYL BENZOATE; ETHYLHEXYLGLYCERIN; TETRASODIUM GLUTAMATE DIACETATE; CITRULLUS LANATUS (WATERMELON) SEED OIL; FRAGRANCE 13576; GLYCERIN; SODIUM HYDROXIDE; WATER; PHENOXYETHANOL; SODIUM HYALURONATE; CI 77491

THE GOLDEN GUARD

Active Ingredients

Avobenzone 3.0%

Octisalate 5.0%

Octocrylene 5.0%

Purpose

Sunscreen

Uses

- helps prevent sunburn
- If used as directed with other sun protection measures (see Directions), decreases the risk of skin cancer and early skin aging caused by the sun

Warnings

For external use only

Do not use

on damaged or broken skin

When using this product

keep out of eyes. Rinse with water to remove.

Stop use and ask a doctor

if rash occurs

Keep out of reach of children.

If swallowed, get medical help or contact a Poison Control Center right away.

Directions

- apply liberally and evenly 15 minutes before sun exposure
- reapply:
  - after 40 minutes of swimming or sweating
  - at least every 2 hours
  - children under 6 months: Ask a doctor
- Sun Protection Measures.Spending time in the sun increases your risk of skin cancer and early aging. To decrease this risk, regularly use a sunscreen with Broad Spectrum SPF value of 15 or higher and other sun protection measures including:
- limit time in the sun, especially from 10 a.m.–2 p.m.
- wear long-sleeve shirts, pants, hats, and sunglasses

Other information

- protect the product in this container from excessive heat and direct sun

Inactive ingredients

Butyloctyl Salicylate, C12-15 Alkyl Benzoate, Caffeine, Caramel, Citrullus Lanatus (Watermelon) Seed Oil, Ethylhexylglycerin, Fragrance, Glycerin, Hibiscus Rosa-Sinensis Flower Extract, Iron Oxides (CI 77491), Mica, Phenoxyethanol, Sodium Hyaluronate, Sodium Hydroxide, Sodium Polyacrylate, Tetrasodium Glutamate Diacetate, Titanium Dioxide, Water

Principal Display Panel

DUNE SUNCARE

THE

GOLDEN GUARD

BROWNING

RADIANCE GEL

SUNCARE FOR

BODY

BROAD SPECTRUM

SPF 30

72 Hour Hydration

Antioxidant Rich

Dermatologist

Approved

Scent: Sea Salt

163 mL

5.5 FL OZ